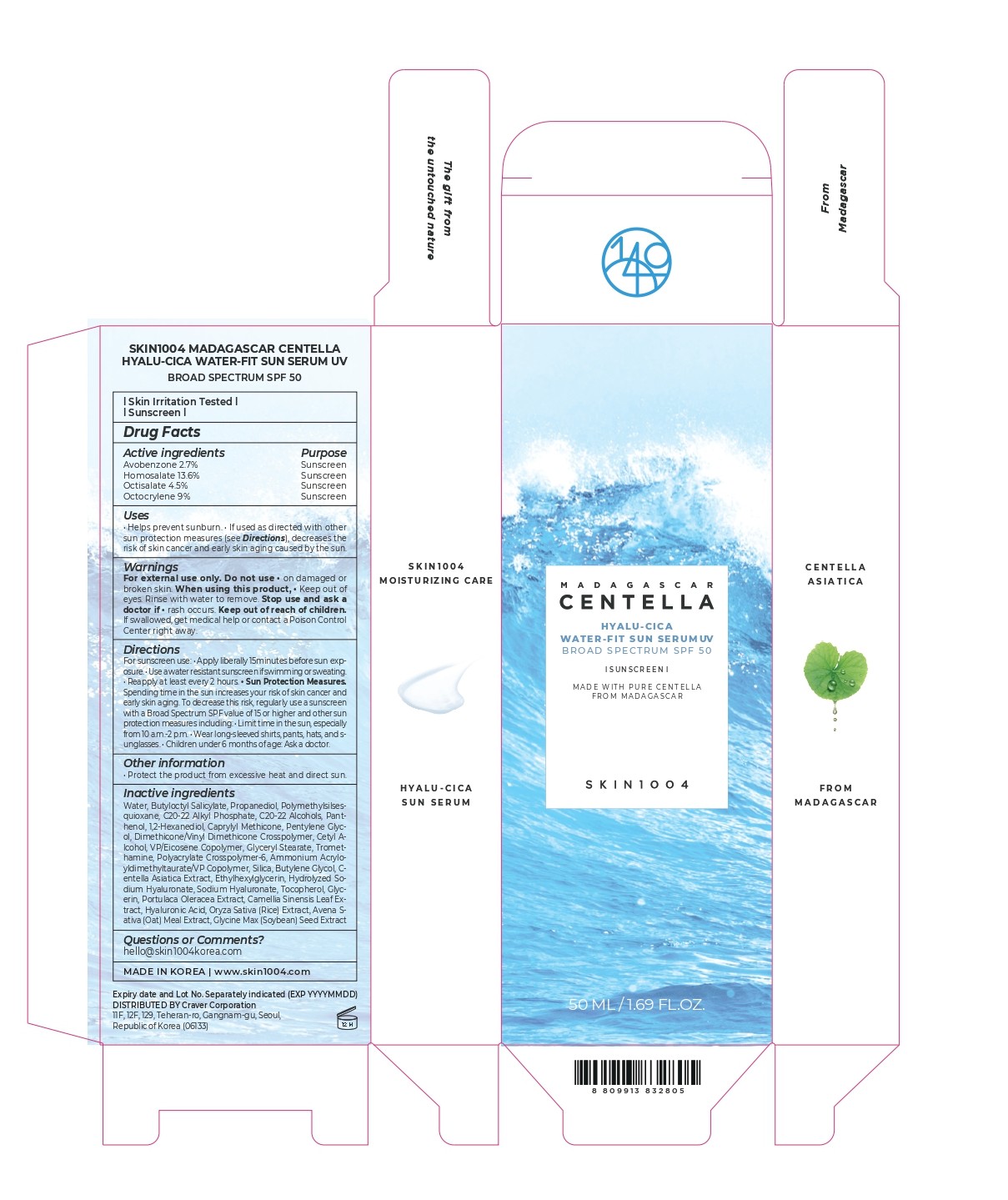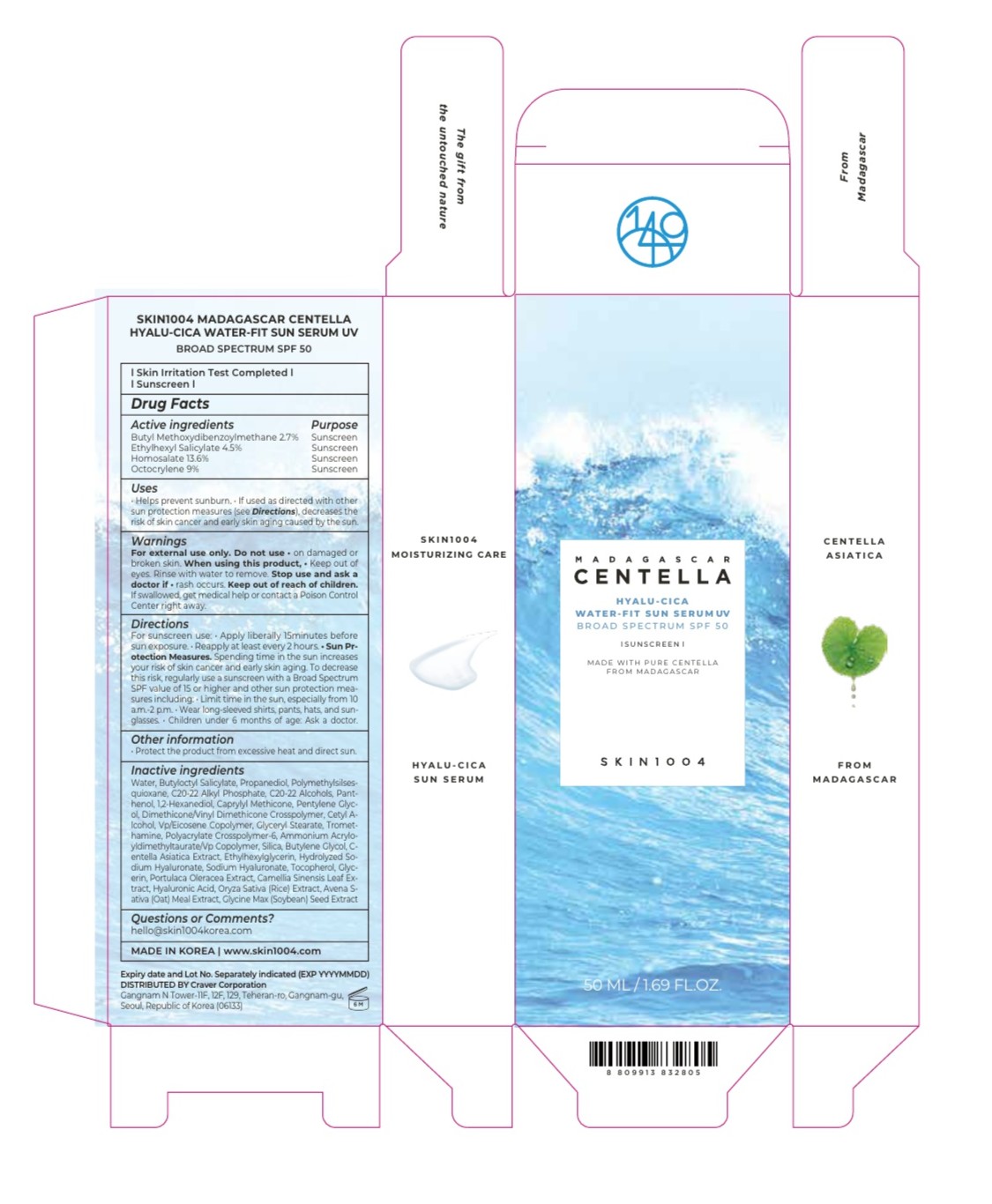 DRUG LABEL: SKIN1004 MADAGASCAR CENTELLA HYALU-CICA WATER-FIT SUN SERUM UV
NDC: 85796-2805 | Form: CREAM
Manufacturer: Craver Corporation
Category: otc | Type: HUMAN OTC DRUG LABEL
Date: 20260208

ACTIVE INGREDIENTS: OCTOCRYLENE 9 g/100 mL; OCTISALATE 4.5 g/100 mL; HOMOSALATE 13.6 g/100 mL; AVOBENZONE 2.7 g/100 mL
INACTIVE INGREDIENTS: TOCOPHEROL; HYALURONIC ACID; BUTYLOCTYL SALICYLATE; PROPANEDIOL; C20-22 ALCOHOLS; CAPRYLYL METHICONE; PENTYLENE GLYCOL; GLYCERYL STEARATE; POLYACRYLATE CROSSPOLYMER-6; BUTYLENE GLYCOL; ETHYLHEXYLGLYCERIN; SODIUM HYALURONATE; PANTHENOL; GLYCERIN; C20-22 ALKYL PHOSPHATE; CETYL ALCOHOL; 1,2-HEXANEDIOL; TROMETHAMINE; AMMONIUM ACRYLOYLDIMETHYLTAURATE/VP COPOLYMER

Warnings

For external use only

Do not use • on damaged or broken skin

When using this product
• keep out of eyes. Rinse with water to remove.

Stop use and ask a doctor if • rash occurs

Keep out of reach of children.
If swallowed, get medical help or contact a Poison Control Center right away.

Directions

For sunscreen use

• Apply liberally 15 minutes before sun exposure
• Reapply at least every 2 hours

Sun Protection Measures. Spending time in the sun increases your risk of skin cancer and early skin aging. To decrease this risk, regularly use a sunscreen with a Broad Spectrum SPF value of 15 or higher and other sun protection measures including:
• Limit time in the sun, especially from 10 a.m.–2 p.m.
• Wear long-sleeved shirts, pants, hats, and sunglasses

• Children under 6 months of age: Ask a doctor

Inactive ingredients

WATER, BUTYLOCTYL SALICYLATE, PROPANEDIOL, POLYMETHYLSILSESQUIOXANE, C20-22 ALKYL PHOSPHATE, C20-22 ALCOHOLS, PANTHENOL, 1,2-HEXANEDIOL, CAPRYLYL METHICONE, PENTYLENE GLYCOL, DIMETHICONE/VINYL DIMETHICONE CROSSPOLYMER, CETYL ALCOHOL, VP/EICOSENE COPOLYMER, GLYCERYL STEARATE, TROMETHAMINE
POLYACRYLATE CROSSPOLYMER-6, AMMONIUM ACRYLOYLDIMETHYLTAURATE/VP COPOLYMER, SILICA, BUTYLENE GLYCOL, CENTELLA ASIATICA EXTRACT, ETHYLHEXYLGLYCERIN, HYDROLYZED SODIUM HYALURONATE, SODIUM HYALURONATE, TOCOPHEROL, GLYCERIN, PORTULACA OLERACEA EXTRACT, CAMELLIA SINENSIS LEAF EXTRACT, HYALURONIC ACID, ORYZA SATIVA (RICE) EXTRACT, AVENA SATIVA (OAT) MEAL EXTRACT, GLYCINE MAX (SOYBEAN) SEED EXTRACT

Uses

• Helps prevent sunburn
• If used as directed with other sun protection measures (see Directions), decreases the risk of skin cancer and early skin aging caused by the sun

KEEP OUT OF REACH OF CHILDREN

If swallowed, get medical help or contact a Poison Control Center right away.

Purpose

Sunscreen